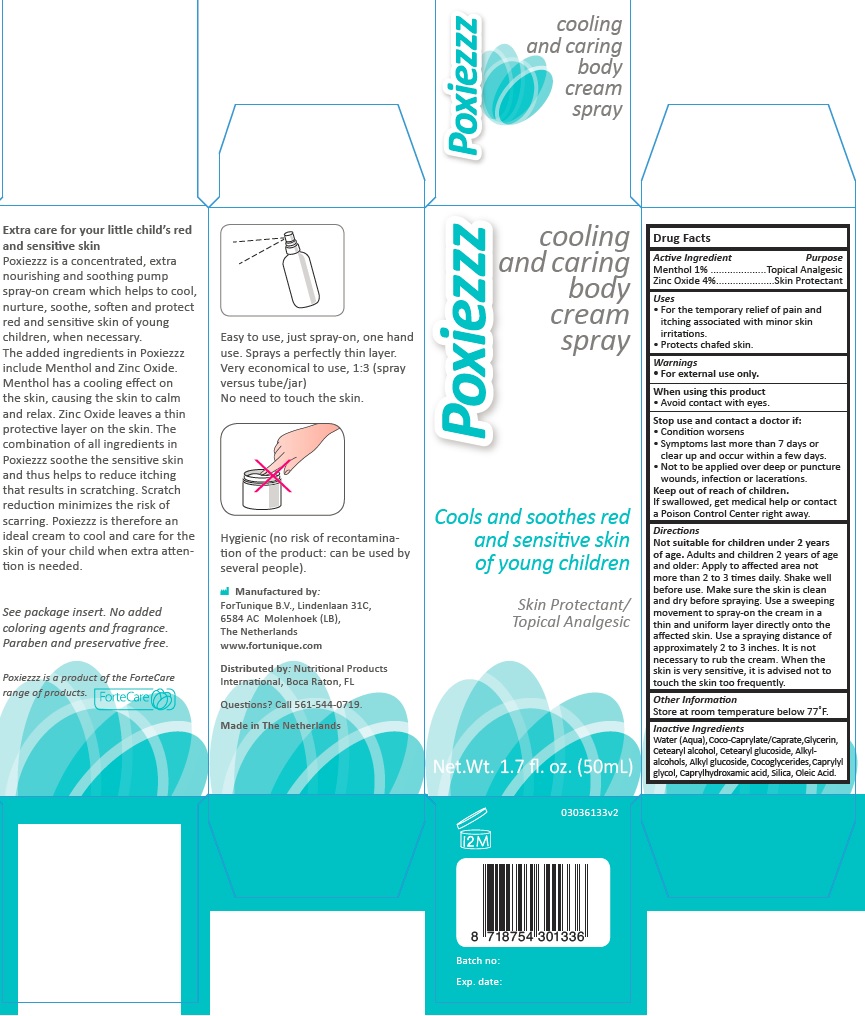 DRUG LABEL: Poxiezzz
NDC: 70359-4106 | Form: SPRAY
Manufacturer: Fortunique B.V.
Category: otc | Type: HUMAN OTC DRUG LABEL
Date: 20161214

ACTIVE INGREDIENTS: MENTHOL, UNSPECIFIED FORM 1 g/100 g; ZINC OXIDE 4 g/100 g
INACTIVE INGREDIENTS: WATER; COCO-CAPRYLATE/CAPRATE; C12-20 ALKYL GLUCOSIDE; COCO-GLYCERIDES; CAPRYLYL GLYCOL; CAPRYLHYDROXAMIC ACID; SILICON DIOXIDE; OLEIC ACID; GLYCERIN; CETOSTEARYL ALCOHOL; CETEARYL GLUCOSIDE; C14-22 ALCOHOLS

Active Ingredients

Menthol 1%

Zinc Oxide 4%

Purpose

Topical Analgesic

Skin Protectant

Uses

For the temporary relief of pain and itching associated with minor skin irritations

Protects chafed skin

Warning

For external use only

When using this product

Avoid contact with eyes

Stop use and contact a Doctor if

Condition worsens .

Symptoms last more than 7 days or clear up and occur within a few days.

Not to be applied over deep a puncture wounds, infection or lacerations

Keep out of reach of children

If swallowed, get medical help or contact a Poison Control Center right away

Directions

Not suitable for children under 2 years of age. Adults and children 2 years of age and older: Apply to affected area no more than 2 to 3 times daily. Shake well before use. Make sure the skin is clean and dry before spraying. Use a sweeping movement to spray-on the cream in a thin and uniform layer directly onto the affected skin. Use a spraying distance of approximately 2 to 3 inches. It is not necessary to rub the cream. When the skin is very sensitive, it is advised not to touch the skin too frequently.

Other information

Store at room temperature bellow 77º F

Inactive Ingredients

Water (aqua)

Coco-Caprylate/Caprate

Glycerin

Cetearyl Alcohol

Cetearyl Glucoside

Alky-Alcohols

Alkyl Glucoside

Cocoglycerides

Caprylylglycol

Caprylhydroxamic Acid

Silica

Oleic Acid